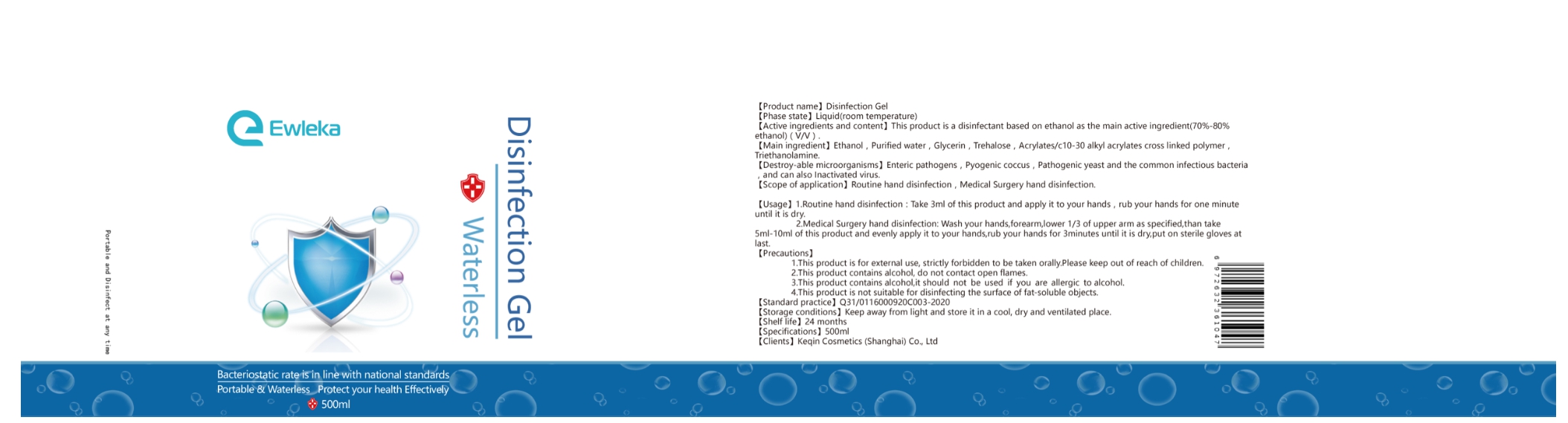 DRUG LABEL: Ewleka Disinfection Gel
NDC: 79239-001 | Form: GEL
Manufacturer: Keqin Cosmetics（shanghai）Co.,Ltd
Category: otc | Type: HUMAN OTC DRUG LABEL
Date: 20200702

ACTIVE INGREDIENTS: ALCOHOL 70 mL/100 mL
INACTIVE INGREDIENTS: GLYCERIN 5 mL/100 mL; WATER 25 mL/100 mL

Alcohol

Alcohol80% v/v Purpose: Antiseptic

Dosage

Take 3ml of this product and apply it to your hands.

for medical surgery hand disinfection：take 5ml- 10ml of this product

Administration: topical

Warnrings

1.This product is for external use, strictly forbidden to be taken orally.Please keep it out of reach of children.

2.This product contains alcohol, do not contact open flames.

3. This product contains alcohol, it should not be used if you are allergic to alhol.

4.This product is not suitable for disinfecting the surface of fat-soluble objects.

Inactive ingredient

water

glycerine

Usage

Take 3ml of this product and apply it to your hands, rub your hands for one minute until it is dry.

Medical Surgery hand disinfection: Wash your hands, lower 1/3of upperarm as specified, than take5ml-10ml of this product and evenly apply it to yourhands , rub your hands for 3 minutes until it is dry, put onsterile gloves at last.

Keep out of reach of children

This product is for external use ,strictly forbidden to be taken orally.

Purpose

It is used for hand disinfection.

Active ingredient

Active ingredient: ethanol

The labeling of Disinfection Gel

500ml NDC ：79239-001